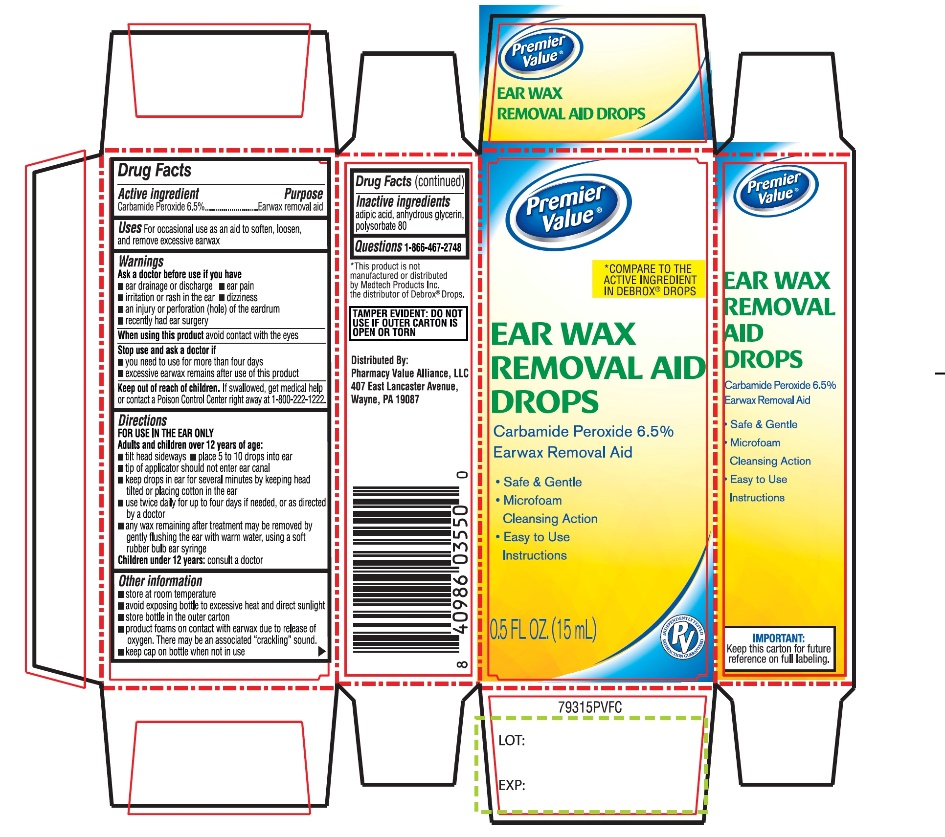 DRUG LABEL: Ear Wax Removal Aid Drops
NDC: 68016-793 | Form: LIQUID
Manufacturer: PHARMACY VALUE ALLIANCE, LLC
Category: otc | Type: HUMAN OTC DRUG LABEL
Date: 20241028

ACTIVE INGREDIENTS: CARBAMIDE PEROXIDE 0.065 mg/1 mL
INACTIVE INGREDIENTS: ADIPIC ACID; GLYCERIN; POLYSORBATE 80

Premier Value Ear Wax Removal Aid Drops

Active ingredient

Carbamide Peroxide 6.5%

Purpose

Earwax removal aid

Uses

For occasional use as an aid to soften, loosen and remove excessive ear wax

Warnings

Ask a doctor before use if you have

- ear drainage or discharge
- ear pain
- irritation or rash in the ear
- dizziness
- an injury or perforation (hole) of the eardrum
- recently had ear surgery

When using this product

avoid contact with the eyes

Stop use and ask a doctor if

- you need to use for more than four days
- excessive ear wax remains after use this product

Keep out of reach of children.

If swallowed, get medical help or contact a Poison Control Center right away at (1-800-222-1222).

Directions

FOR USE IN THE EAR ONLY.

- Adults and children over 12 years of age:
- tilt head sideways
- place 5 to 10 drops into ear canal.
- tip of applicator should not enter ear canal.
- keep drops in ear for several minutes by keeping head tilted or placing cotton in the ear.
- use twice daily for up to four days if needed, or as directed by a doctor.
- any wax remaining after treatment may be removed by gently flushing the ear with warm water, using a soft rubber bulb ear syringe.

Children under 12 years of age: consult a doctor.

Other information

- Store at room temperature
- Avoid exposing bottle to excessive heat and direct sunlight
- Store bottle in the outer carton
- Product foams on contact with earwax due to release of oxygen. There may be an associated “cracking” sound.
- Keep cap on bottle when not in use

Inactive ingredients

adipic acid, anhydrous glycerin, polysorbate 80.

Questions or comments?

1-866-467-2748

PRINCIPAL DISPLAY PANEL

Premier Value®

NDC 68016-793-15

*COMPARE TO THE ACTIVE INGREDIENT IN DEBROX® DROPS

EAR WAX REMOVAL AID DROPS KIT
Carbamide Peroxide 6.5%

Ear Wax Removal Aid

- Safe & Gentle
- Microfoam Cleansing Action
- Easy to use Instructions

NET WT 0.5 FL OZ (15 mL)

This kit include soft rubber bulb ear syringe and drops

TAMPER EVIDENT: DO NOT USE IF OUTER CARTON IS OPEN OR TORN

IMPORTANT: Keep the carton for future reference on full labeling.

Distributed BY:

Pharmacy Value Alliance, LLC

407 East Lancaster Avenue,

Wayne, PA 19087

*This product is not manufactured or distributed by Medtech Products Inc. the distributor of Debrox® Drops.